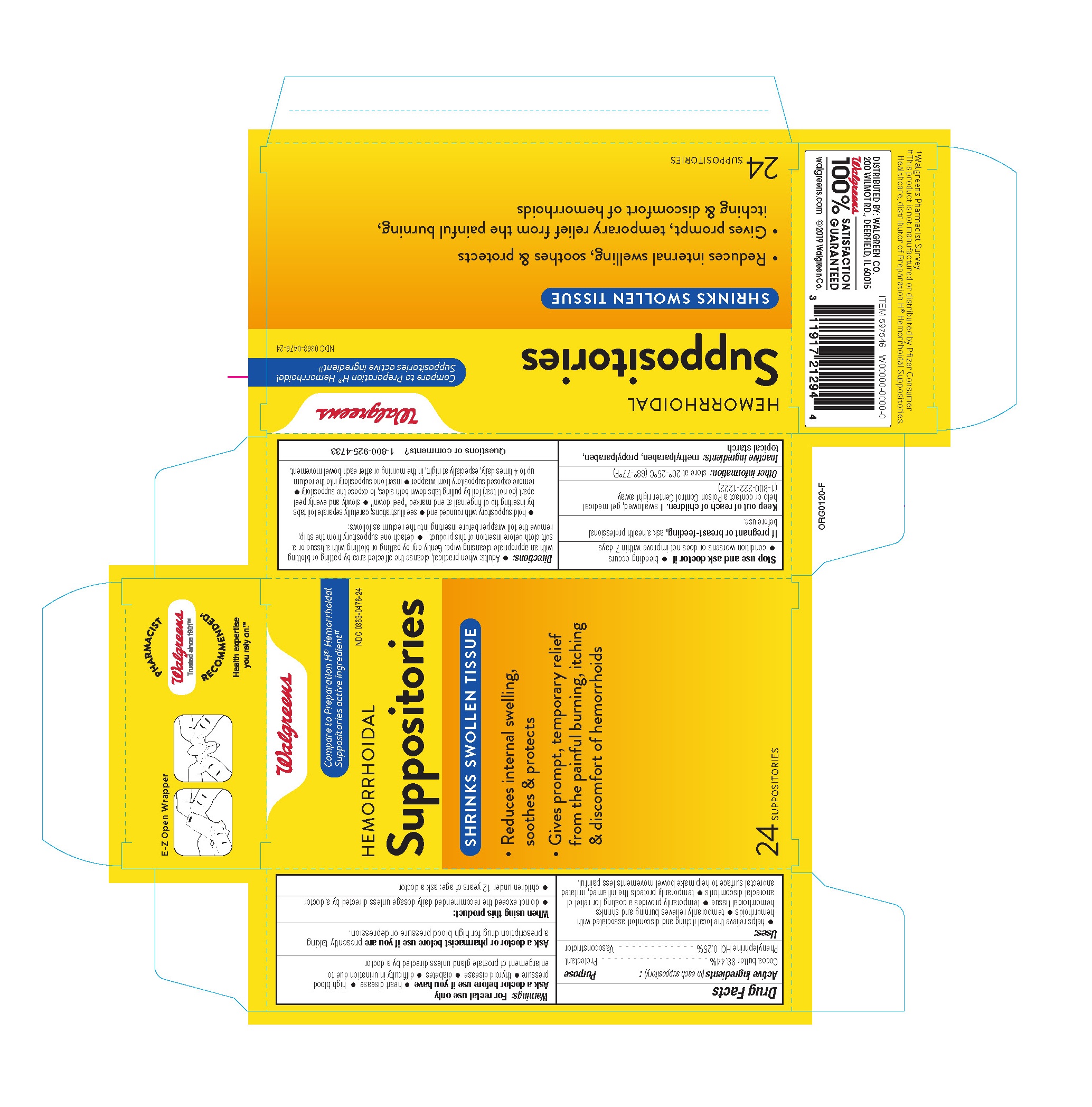 DRUG LABEL: Walgreens Hemorrhoidal
NDC: 0363-0476 | Form: SUPPOSITORY
Manufacturer: Walgreens
Category: otc | Type: HUMAN OTC DRUG LABEL
Date: 20260114

ACTIVE INGREDIENTS: COCOA BUTTER 2211 mg/1 1; PHENYLEPHRINE HYDROCHLORIDE 6.25 mg/1 1
INACTIVE INGREDIENTS: METHYLPARABEN; PROPYLPARABEN; MODIFIED CORN STARCH (1-OCTENYL SUCCINIC ANHYDRIDE)

WALGREENS HEMORRHOIDAL SUPPOSITORIES

Drug Facts

Active Ingredients Purpose

Cocoa butter 88.44%...................................................................Protectant

Phenylephrine hydrochloride 0.25%..............................................Vasoconstrictor

Uses

- helps relieve the local itching and discomfort associated with hemorrhoids
- temporarily relieves burning and shrinks hemorrhoidal tissue
- temporarily provides a coating for relief of anorectal discomforts
- temporarily protects the inflamed, irritated anorectal surface to help make bowel movements less painful

Warnings

For rectal use only

Ask a doctor or pharmacist before use if you are presently taking a prescription drug for high blood pressure or depression

Ask a doctor before use if you have

-heart disease -high blood pressure

-thyroid disease -diabetes

-difficulty in urination due to enlargement of the prostate gland unless directed by a doctor

When using this product do not exceed the recommended daily dosage unless directed by a doctor

Stop use and ask a doctor if bleeding occurs or if condition worsens or does not improve within 7 days

If pregnant or breastfeeding, ask a health professional before use.

Keep out of reach of children. If swallowed, get medical help or contact a Poison Control Center right away. (1-800-222-1222)

Directions: Adults

-when practical, cleanse the affected area by patting or blotting with an appropriate cleansing wipe. Gently dry by patting or blotting with a tissue or a soft cloth before insertion of this product.

-detach one suppository from the strip; remove the foil wrapper before inserting into the rectum as follows:

-hold suppository with rounded end up

-as shown, carefully separate foil tabs by inserting tip of fingernail at end marked "peel down"

-slowly and evenly peel apart (do not tear) foil by pulling tabs down both sides, to expose from wrapper

-insert on suppository into the rectum up to 4 times daily, especially at night, in the morning or after each bowel movement

-children under 12 years of age: ask a doctor

Other information

Store at 20oC-25oC (68oF-77oF)

Inactive ingredients

corn starch, methylparaben, propylparaben